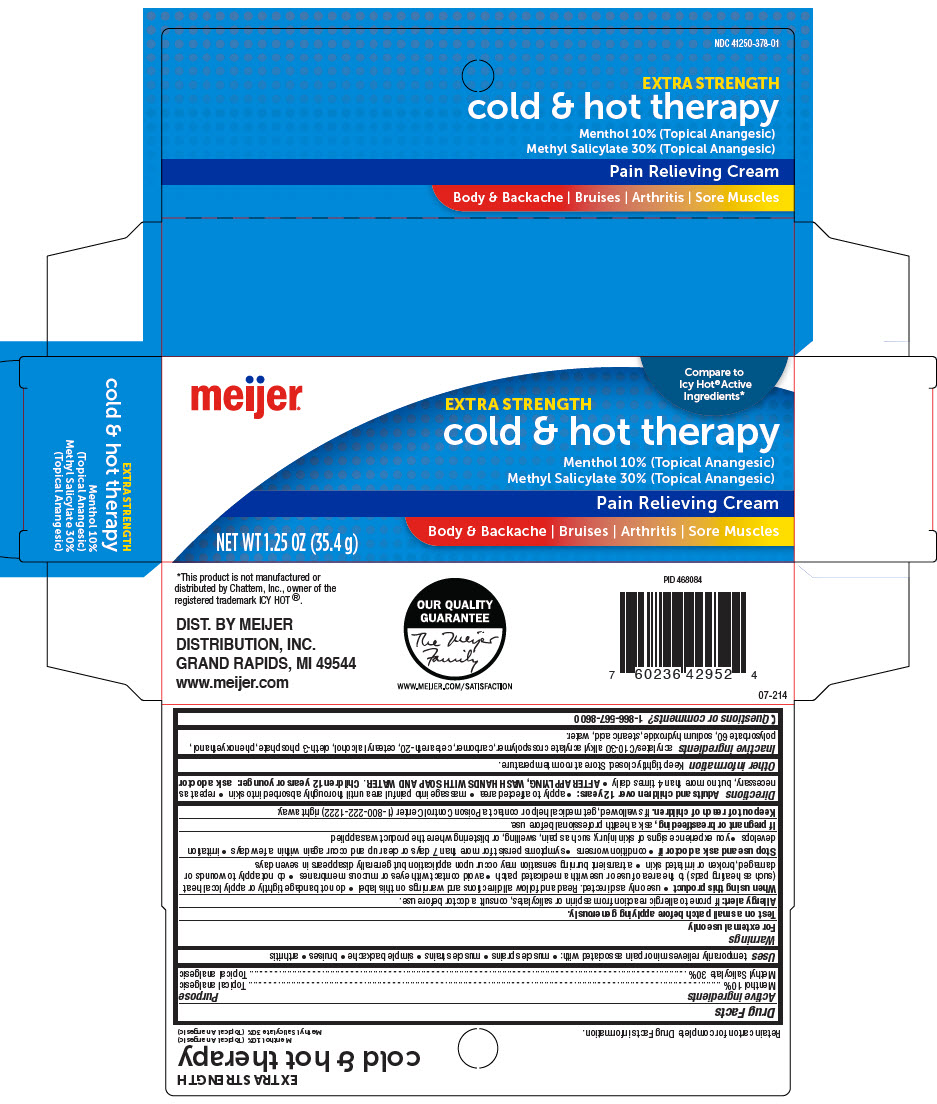 DRUG LABEL: Meijer Extra Strength Cold And Hot TherapyPain Relieving
NDC: 41250-378 | Form: CREAM
Manufacturer: Meijer Distribution, Inc
Category: otc | Type: HUMAN OTC DRUG LABEL
Date: 20241107

ACTIVE INGREDIENTS: Menthol, Unspecified Form 100 mg/1 g; Methyl Salicylate 300 mg/1 g
INACTIVE INGREDIENTS: Carbomer Interpolymer Type A (Allyl Sucrose Crosslinked); Carbomer Homopolymer, Unspecified Type; Polyoxyl 20 Cetostearyl Ether; Cetostearyl Alcohol; Oleth-3 Phosphate; Phenoxyethanol; Polysorbate 60; Sodium Hydroxide; Stearic Acid; Water

Meijer® Extra Strength Cold & Hot TherapyPain Relieving Cream
Topical Analgesic

Drug Facts

ACTIVE INGREDIENT

Active ingredients | Purpose
Menthol 10% | Topical analgesic
Methyl Salicylate 30% | Topical analgesic

Uses

temporarily relieves minor pain associated with:

- muscle sprains
- muscle strains
- simple backache
- bruises
- arthritis

Warnings

For external use only

Test on a small patch before applying generously.

Allergy alert

If prone to allergic reaction from aspirin or salicylates, consult a doctor before use.

When using this product

- use only as directed. Read and follow all directions and warnings on this label
- do not bandage tightly or apply local heat (such as heating pads) to the area of use or use with a medicated patch
- avoid contact with eyes or mucous membranes
- do not apply to wounds or damaged, broken or irritated skin
- a transient burning sensation may occur upon application but generally disappears in seven days

Stop use and ask a doctor if

- condition worsens
- symptoms persist for more than 7 days or clear up and occur again within a few days
- irritation develops
- you experience signs of skin injury, such as pain, swelling, or blistering where the product was applied

PREGNANCY OR BREAST FEEDING

If pregnant or breastfeeding, ask a health professional before use.

Keep out of reach of children. If swallowed, get medical help or contact a Poison Control Center (1-800-222-1222) right away.

Directions

Adults and children over 12 years:

- apply to affected area
- massage into painful area until thoroughly absorbed into skin
- repeat as necessary, but no more than 4 times daily
- AFTER APPLYING, WASH HANDS WITH SOAP AND WATER.

Children 12 years or younger: ask a doctor

Other information

Keep tightly closed. Store at room temperature.

Inactive ingredients

acrylates/C10-30 alkyl acrylate crosspolymer, carbomer, ceteareth-20, cetearyl alcohol, oleth-3 phosphate, phenoxyethanol, polysorbate 60, sodium hydroxide, stearic acid, water.

Questions or comments?

1-866-567-8600

DIST. BY MEIJER
DISTRIBUTION, INC.
GRAND RAPIDS, MI 49544

PRINCIPAL DISPLAY PANEL - 35.4 g Tube Carton

Compare to
Icy Hot®Active
Ingredients*

meijer®

EXTRA STRENGTH
cold & hot therapy

Menthol 10% (Topical Anangesic)
Methyl Salicylate 30% (Topical Anangesic)

Pain Relieving Cream

Body & Backache | Bruises | Arthritis | Sore Muscles

NET WT 1.25 OZ (35.4 g)